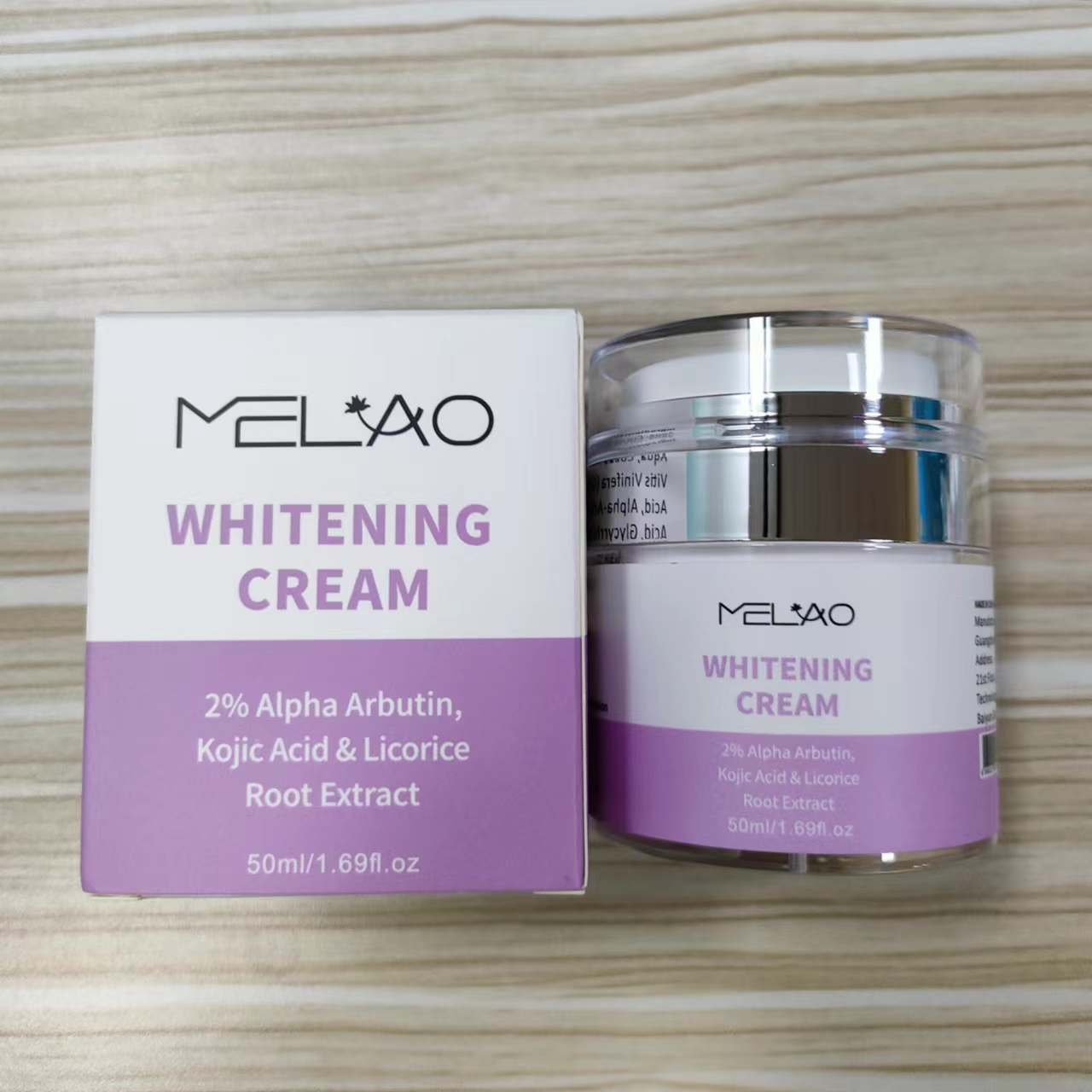 DRUG LABEL: MELAO Whitening Cream
NDC: 74458-134 | Form: CREAM
Manufacturer: Guangzhou Yilong Cosmetics Co., Ltd
Category: otc | Type: HUMAN OTC DRUG LABEL
Date: 20241119

ACTIVE INGREDIENTS: ALPHA-ARBUTIN 2 g/100 mL; KOJIC ACID 0.7 g/100 mL; GLYCYRRHIZA GLABRA (LICORICE) ROOT EXTRACT 0.5 g/100 mL
INACTIVE INGREDIENTS: TOCOPHEROL; TETRASODIUM GLUTAMATE DIACETATE; AQUA; PHENOXYETHANOL; XANTHAN GUM; VITIS VINIFERA (GRAPE) SEED OIL; COCOS NUCIFERA (COCONUT) OIL; STEARIC ACID; GLYCERIN

MELAO WHITENING CREAM

ACTIVE INGREDIENT

Alpha-Arbutin

Kojic Acid

Glycyrrhiza Glabra (Licorice) Root Extract

INACTIVE INGREDIENT

Aqua

Cocos Nucifera (Coconut) Oil

Vitis Vinifera (Grape) Seed Oil

Stearic Acid

Glycerin

Xanthan Gum

Tocopherol

Phenoxyethanol

Tetrasodium Glutamate Diacetate

PURPOSE

Whitening.

INDICATIONS AND USAGE

Wash and pat skin dry. Apply a small
amount to entire area. Gently massage into the skin. Should be
used twice a day for optimal results.

WARNINGS

For external use only.

Stop use and ask a doctor if rash occurs.

Do not use on damaged or broken skin.

When using this product keep out of eyes. Rinse with water to remove.

Keep out of reach of children. If swallowed, get medical help or contact a Poison Control Center right away.

DOSAGE AND ADMINISTRATION

Wash and pat skin dry. Apply a small
amount to entire area. Gently massage into the skin. Should be
used twice a day for optimal results.